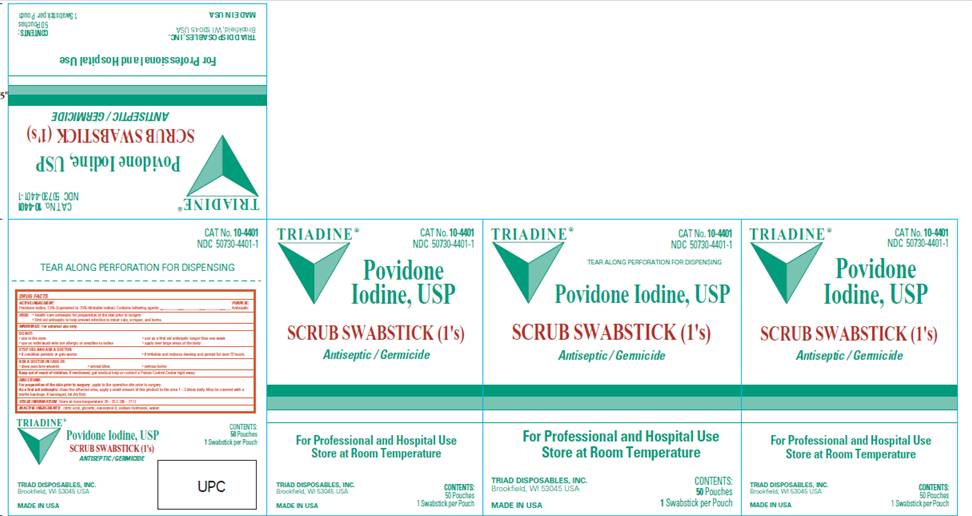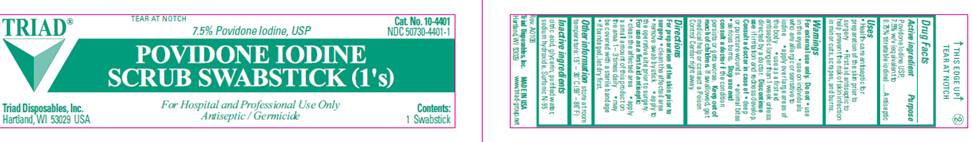 DRUG LABEL: Povidone-Iodine Scrub Swabstick
NDC: 50730-4401 | Form: SOLUTION
Manufacturer: H and P Industries, Inc. dba Triad Group
Category: otc | Type: HUMAN OTC DRUG LABEL
Date: 20091124

ACTIVE INGREDIENTS: povidone-iodine .075 mg/1 mL
INACTIVE INGREDIENTS: citric acid monohydrate; glycerin; nonoxynol-9; polyethylene glycol 300; sodium hydroxide; sodium phosphate, monobasic, monohydrate; water

DRUG FACTS

ACTIVE INGREDIENT

Povidone Iodine USP 7.5% w/v (equivalent to 0.75% titratable iodine)

PURPOSE

Antiseptic

USES

- Health Care Antiseptic for preparation of the skin prior to surgery

- First Aid Antiseptic to help prevent the risk of infection in minor cuts, scrapes and burns

WARNINGS

For external use only.

Do not

- use in the eyes
- apply over large areas of the body
- use on individuals who are allergic or sensitive to iodine
- use as a first aid antiseptic for longer than 1 week unless directed by a doctor

Ask a doctor in case of

- deep or puncture wounds
- animal bites
- serious burns

Stop use and ask a doctor

- if condition persists for more than 72 hours
- if irritation and redness develop

Keep out of reach of children

If swallowed, get medical help or contact a Poison Control Center right away.

DIRECTIONS

For preparation of the skin prior to surgery

- clean the affected area
- apply to the operative site prior to surgery

As a first aid antiseptic

- clean the affected area
- apply a small amount of this product to the area 1-3 times daily
- may be covered with a sterile bandage
- if bandaged, let dry first

OTHER INFORMATION

Store at room temperature 15° - 30° C (59° - 86° F)

INACTIVE INGREDIENTS

citric acid, glycerin, purified water, sodium hydroxide, Surfonic N-95

LABEL INFORMATION

TRIAD
Cat. No. 10-4401
NDC 50730-4401-1
7.5% Povidone Iodine, USP
POVIDONE IODINE
SCRUB SWABSTICK (1's)
Triad Disposables, Inc.
Hartland, WI 53029 USA
For Hospital and Professional Use Only
Antiseptic / Germicide
Contents:
1 Swabstick

CARTON INFORMATION

TRIADINE
Cat. No. 10-4401
NDC 50730-4401-1
Povidone Iodine, USP
POVIDONE IODINE
SCRUB SWABSTICK (1's)

Antiseptic / Germicide

Triad Disposables, Inc.
Brookfield, WI 53045

MADE IN USA
For Hospital and Professional Use
Store at Room Temperature
Contents:
50 Pouches
1 Swabstick per Pouch